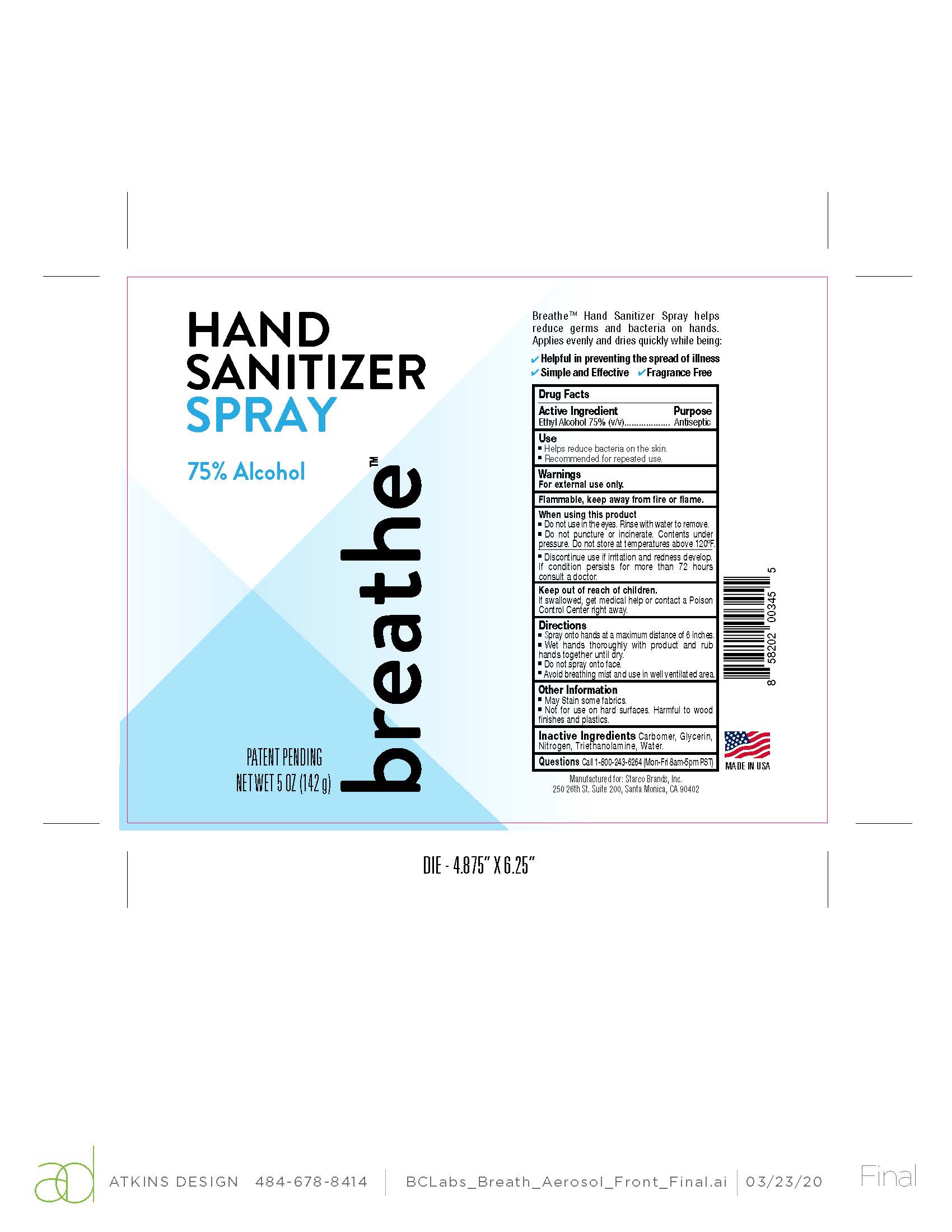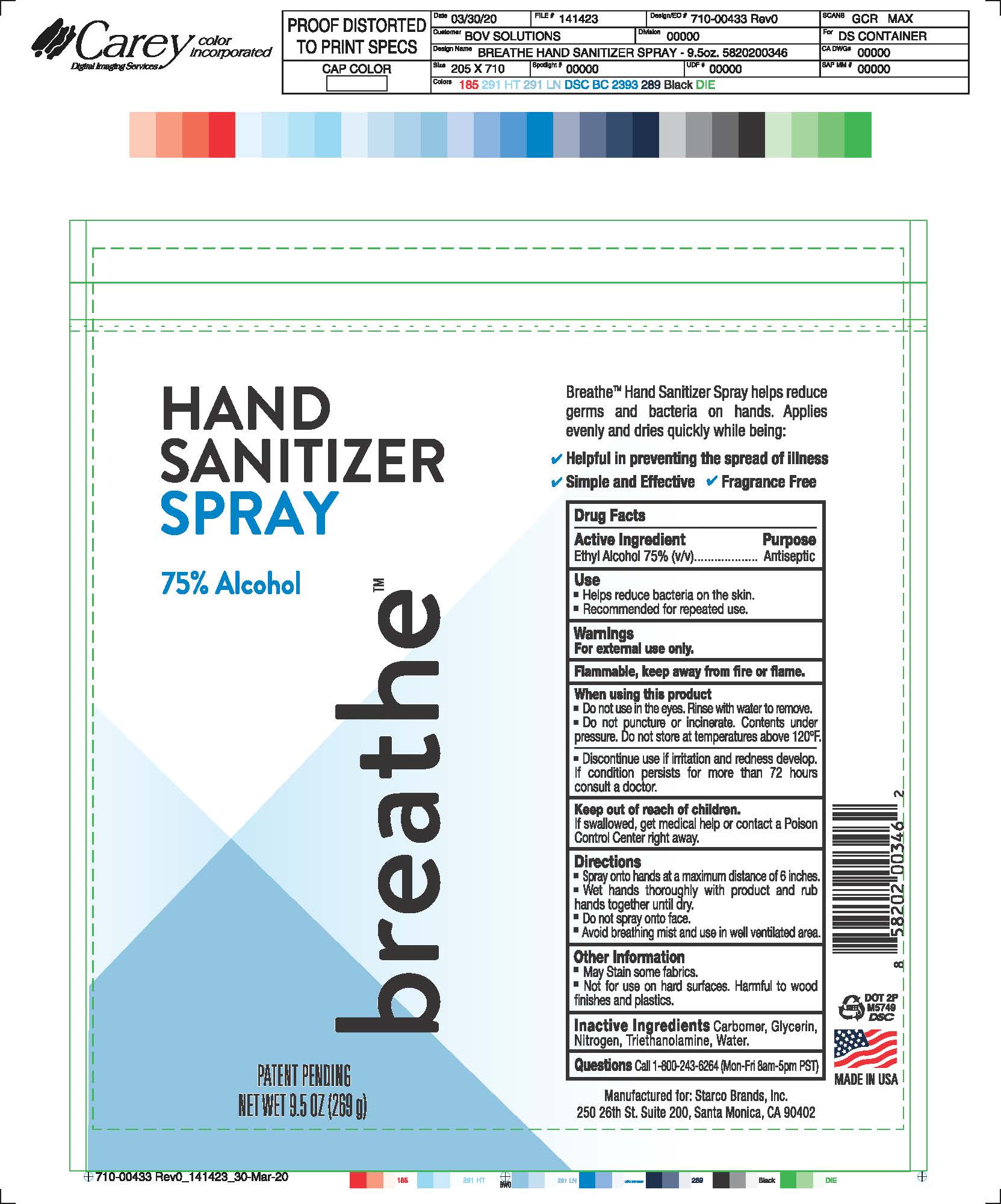 DRUG LABEL: Liauid Hand Sanitizer
NDC: 52313-1256 | Form: SPRAY
Manufacturer: Sklar BOV Solutions, Inc
Category: otc | Type: HUMAN OTC DRUG LABEL
Date: 20220131

ACTIVE INGREDIENTS: ALCOHOL 0.75 mL/1 mL
INACTIVE INGREDIENTS: CARBOMER 980; NITROGEN; GLYCERIN

Liquid Hand Sanitizer

Active Ingredient Purpose

Ethyl Alcohol 75% (V/V) Atniseptic

Use

*Helps reduce bacteria on the skin

*Recommended for repeated use

Warnings

For External Use Only

Flammable

Keep away from fire or flame.

.

Keep put of reach of children.

If swallowed, get medical help or contact a Poison Control Center right away

When using this product

* Do not use in the eyes. Rince with water to remove.

* Do not puncture or incinirate. Contents under pressure. Do not store at temperatures above 120ºF.

Discontinure use if irritation and redness develop. If condition presists for more than 72 hours, consult a doctor.

Directions

*Spray onto hands at a maximum distance of 6 inches

*Wet hands throughly with product and rub hands together till dry.

*Do not apply to face

*Avoid breathing mist and use in well ventilated area.

WARNINGS AND PRECAUTIONS

Other Informaton

* May Stain some Fabrics

*Do not use on hard surfaces. Harmful to wood finishes and plastics

Inactive Ingredients

Carbomer, Glycerin, Nitrogen, Triethanolamine, Water

Questions

Call 1-800-243-6264 (Mon-Fri-8am-5pm PST)

PACKAGE LABEL

269 ML NDC 52313-1256-2